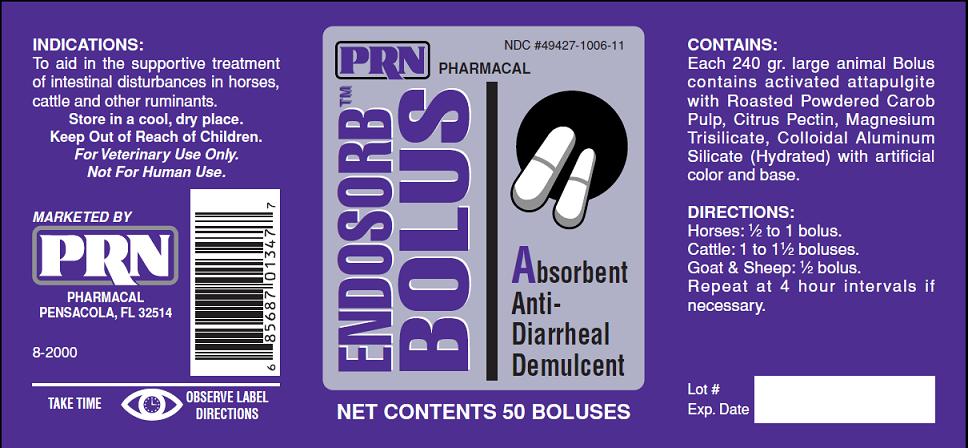 DRUG LABEL: Endosorb Bolus
NDC: 49427-006 | Form: TABLET
Manufacturer: Pegasus Laboratories, Inc.
Category: animal | Type: OTC ANIMAL DRUG LABEL
Date: 20111006

ACTIVE INGREDIENTS: ATTAPULGITE 3270 mg/1 1; KAOLIN 130 mg/1 1; CAROB 440 mg/1 1; PECTIN, CITRUS 290 mg/1 1; MAGNESIUM TRISILICATE 150 mg/1 1

INDICATIONS:

To aid in the supportive treatment of intestinal disturbances in horses, cattle and other ruminants

DIRECTIONS:

Horses: ½ to 1 bolus.
Cattle: 1 to 1½ boluses.
Goat and Sheep: ½ bolus.
Repeat at 4 hour intervals if necessary

CONTAINS:

Each 240 grain large animal Bolus contains activated attapulgite with Roasted Powdered Carob Pulp, Citrus Pectin, Magnesium Trisilicate, Colloidal Aluminum Silicate (Hydrated) with artificial color and base.

STORAGE:

Store in a cool, dry place.

WARNINGS:

Keep Out of Reach of Children.

For Veterinary Use Only.

Not For Human Use.

PACKAGE LABEL

PRN PHARMACAL NDC # 49427-1006-11
ENDOSORB BOLUS TM
Absorbant Anti-Diarrheal Demulcent

NET CONTENTS 50 BOLUSES